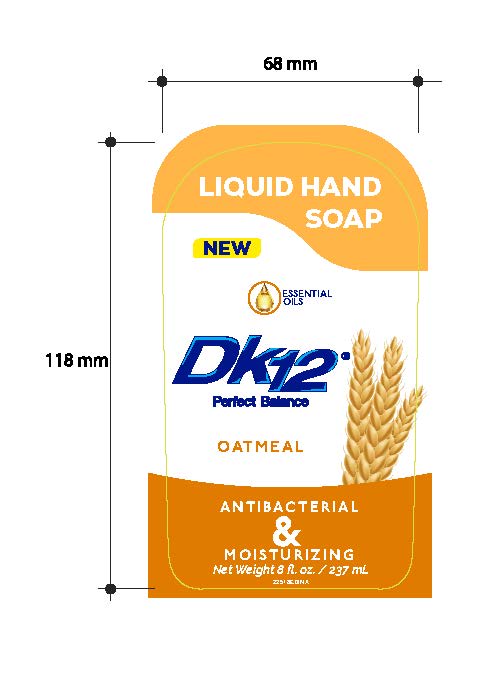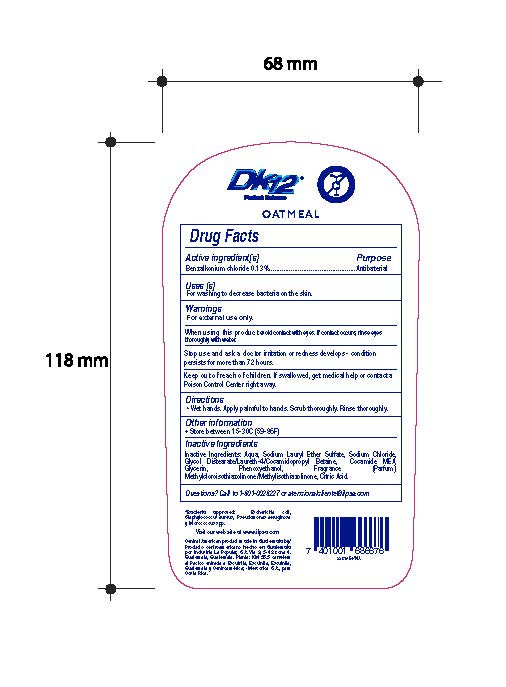 DRUG LABEL: DK12 Liquid Hand Oatmeal
NDC: 62476-006 | Form: LIQUID
Manufacturer: Industria La Popular, S.A.
Category: otc | Type: HUMAN OTC DRUG LABEL
Date: 20241202

ACTIVE INGREDIENTS: BENZALKONIUM CHLORIDE 0.65 g/500 mL
INACTIVE INGREDIENTS: METHYLCHLOROISOTHIAZOLINONE; SODIUM LAURYL SULFATE; WATER; GLYCERIN; METHYLISOTHIAZOLINONE; ANHYDROUS CITRIC ACID; SODIUM CHLORIDE; GLYCOL DISTEARATE; PHENOXYETHANOL; COCAMIDOPROPYL BETAINE; LAURETH-4; COCAMIDE

DK12 Liquid Hand Soap Oatmeal

Active Ingredient

Benzalkonium Chloride 0.13%

Purpose

Antibacterial

Uses

For washing to decrease bacteria on the skin

Warnings

For External Use only.

When using this product

avoid contact with eyes. If contact occurs, rinse eyes thoroughly with water.

Stop use and ask a doctor

irritation or redness develops - condition persists for more than 72 hours.

Keep out of reach of children.

If swallowed, get medical help or contact a Poison Control Center right away

Directions

Wet hands. Apply palmful to hands. Scrub thoroughly. Rinse thoroughly.

Other Information

Store between 15-30C (59-86F)

Inactive Ingredients

Aqua, Sodium Lauryl Ether Sulfate, Sodium Chloride, Glycol Distearate/Laureth-4/Cocamidopropyl Betaine, Cocamide MEA, Glycerin, Phenoxyethanol, Fragrance, Methylchloroisothiazolinone/Methylisothiazolinone, Citric Acid